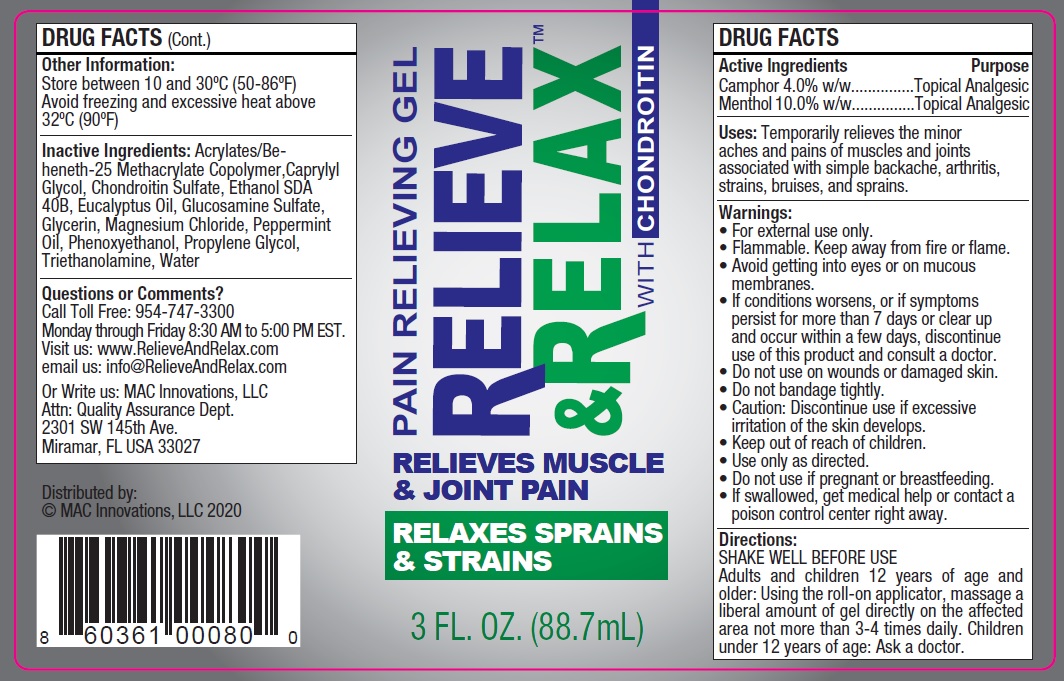 DRUG LABEL: Relieve and Relax Pain Relieving
NDC: 81790-001 | Form: GEL
Manufacturer: MAC Innovations, LLC
Category: otc | Type: HUMAN OTC DRUG LABEL
Date: 20251229

ACTIVE INGREDIENTS: CAMPHOR (SYNTHETIC) 40 mg/1 mL; MENTHOL 100 mg/1 mL
INACTIVE INGREDIENTS: CAPRYLYL GLYCOL; EUCALYPTUS OIL; GLUCOSAMINE SULFATE; GLYCERIN; MAGNESIUM CHLORIDE; PEPPERMINT OIL; PHENOXYETHANOL; PROPYLENE GLYCOL; TROLAMINE; WATER

Relieve and Relax Pain Relieving

Active Ingredients

Camphor 4.0% w/w

Menthol 10.0% w/w

Purpose

Topical Analgesic

Uses:

Temporarily relieves the minor aches and pains of muscles and joints associated with simple backache, arthritis, strains, bruises, and sprains.

Warnings:

• For external use only.

• Flammable, Keep away from fire or flame.

• Avoid getting into eyes or on mucous membranes.

• If conditions worsens, or if symptoms persist for more than 7 days or clear up and occur within a few days, discontinue use of this product and consult a doctor.

Do not use

• on wounds or damaged skin.

• Do not bandage tightly. • Caution: Discontinue use if excessive irritation of the skin develops.

Keep out of reach of children.

• Use only as directed. • Do not use if pregnant or breastfeeding. • If swallowed, get medical help or contact a poison control center right away.

Directions:

SHAKE WELL BEFORE USE Adults and children 12 years of age and older: Using the roll-on applicator, massage a liberal amount of gel directly on the affected area not more than 3-4 times daily. Children under 12 years of age: Ask a doctor.

Other Information:

Store between 10 and 30ºC (50-86ºF) Avoid freezing and excessive heat above 32ºC (90ºF)

Inactive Ingredients:

Acrylates/Beheneth- 25 Methacrylate Copolymer,Caprylyl Glycol, Chondroitin Sulfate, Ethanol SDA 40B, Eucalyptus Oil, Glucosamine Sulfate, Glycerin, Magnesium Chloride, Peppermint Oil, Phenoxyethanol, Propylene Glycol, Triethanolamine, Water

Questions or Comments?

Call Toll Free: 954-747-3300 Monday through Friday 8:30 AM to 5:00 PM EST. Visit us: www.RelieveAndRelax.com email us: info@RelieveAndRelax.com Or Write us: MAC Innovations, LLC Attn: Quality Assurance Dept. 2301 SW 145th Ave. Miramar, FL USA 33027